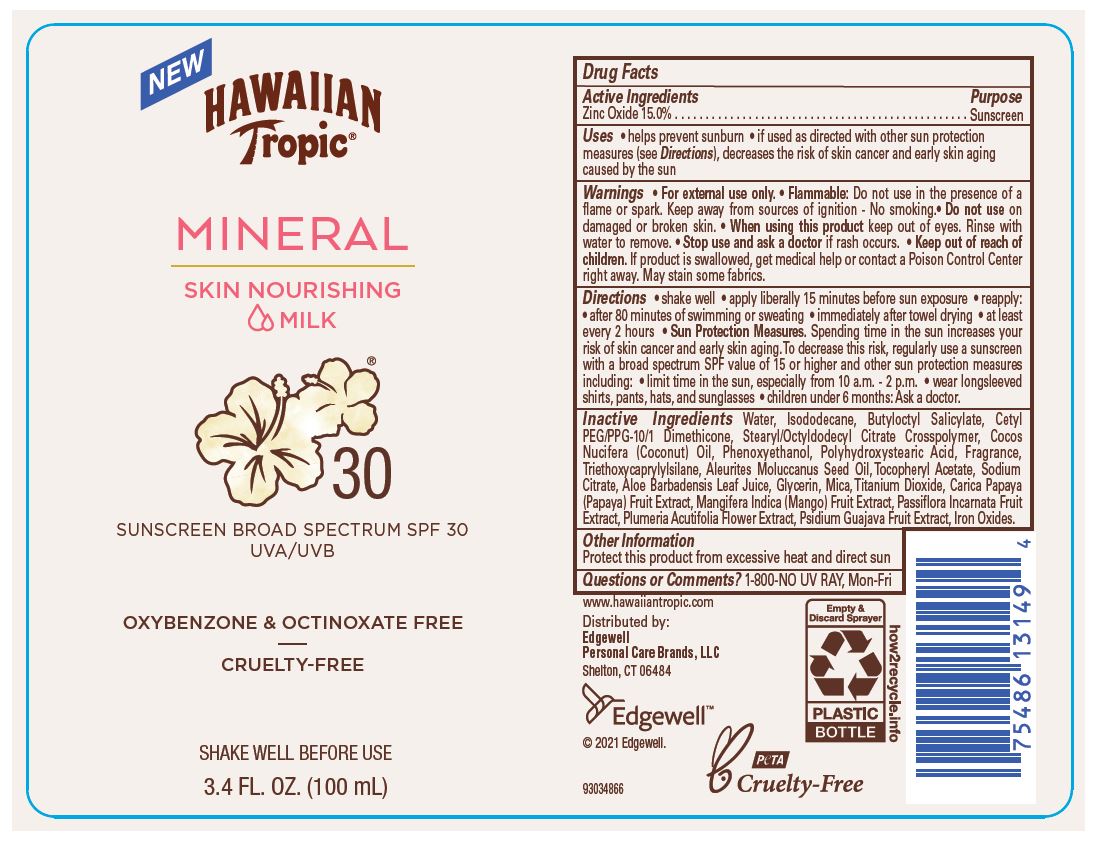 DRUG LABEL: Hawaiian Tropic Mineral Skin Nourishing Milk Sunscreen Broad Spectrum SPF 30
NDC: 63354-421 | Form: LOTION
Manufacturer: Edgewell Personal Care Brands LLC
Category: otc | Type: HUMAN OTC DRUG LABEL
Date: 20241101

ACTIVE INGREDIENTS: ZINC OXIDE 15 g/100 g
INACTIVE INGREDIENTS: WATER; ISODODECANE; COCONUT OIL; ALOE VERA LEAF; TITANIUM DIOXIDE; PAPAYA; PLUMERIA RUBRA FLOWER; BUTYLOCTYL SALICYLATE; CETYL PEG/PPG-10/1 DIMETHICONE (HLB 2); PHENOXYETHANOL; TRIETHOXYCAPRYLYLSILANE; STEARYL/OCTYLDODECYL CITRATE CROSSPOLYMER; ANHYDROUS TRISODIUM CITRATE; MANGO; GLYCERIN; MICA; PASSIFLORA INCARNATA FRUIT; GUAVA; KUKUI NUT OIL; FERRIC OXIDE YELLOW; POLYHYDROXYSTEARIC ACID (2300 MW); .ALPHA.-TOCOPHEROL ACETATE

Active Ingredients

Zinc Oxide 15.0%

Purpose

Sunscreen

Uses

• helps prevent sunburn • if used as directed with other sun protection measures (see Directions), decreases the risk of skin cancer and early skin aging caused by the sun

Warnings

• For external use only.

Flammable: Do not use in the presence of a flame or spark. Keep away from sources of ignition - No smoking.

May stain some fabrics.

Do not use

on damaged or broken skin.

When using this product

keep out of eyes. Rinse with water to remove.

Stop use and ask a doctor

if rash occurs.

Keep out of reach of children.

If product is swallowed, get medical help or contact a Poison Control Center right away.

Directions

• shake well • apply liberally 15 minutes before sun exposure • reapply: • after 80 minutes of swimming or sweating • immediately after towel drying • at least every 2 hours • Sun Protection Measures. Spending time in the sun increases your risk of skin cancer and early skin aging. To decrease this risk, regularly use a sunscreen with a broad spectrum SPF value of 15 or higher and other sun protection measures including: • limit time in the sun, especially from 10 a.m. - 2 p.m. • wear longsleeved shirts, pants, hats, and sunglasses • children under 6 months: Ask a doctor.

Inactive Ingredients

Water, Isododecane, Butyloctyl Salicylate, Cetyl PEG/PPG-10/1 Dimethicone, Stearyl/Octyldodecyl Citrate Crosspolymer, Cocos Nucifera (Coconut) Oil, Phenoxyethanol, Polyhydroxystearic Acid, Fragrance, Triethoxycaprylylsilane, Aleurites Moluccanus Seed Oil, Tocopheryl Acetate, Sodium Citrate, Aloe Barbadensis Leaf Juice, Glycerin, Mica, Titanium Dioxide, Carica Papaya (Papaya) Fruit Extract, Mangifera Indica (Mango) Fruit Extract, Passiflora Incarnata Fruit Extract, Plumeria Acutifolia Flower Extract, Psidium Guajava Fruit Extract, Iron Oxides.

Other Information

Protect this product from excessive heat and direct sun

Questions or Comments?

1-800-NO UV RAY, Mon-Fri

Principal Display Panel

NEW
HAWAIIAN
TROPIC(R)
MINERAL
SKIN NOURISHING
MILK
30
SUNSCREEN BROAD SPECTRUM SPF30
UVA/UVB
OXYBENZONE & OCTINOXATE FREE
CRUELTY-FREE
SHAKE WELL BEFORE USE
3.4 FL. OZ. (100 mL)